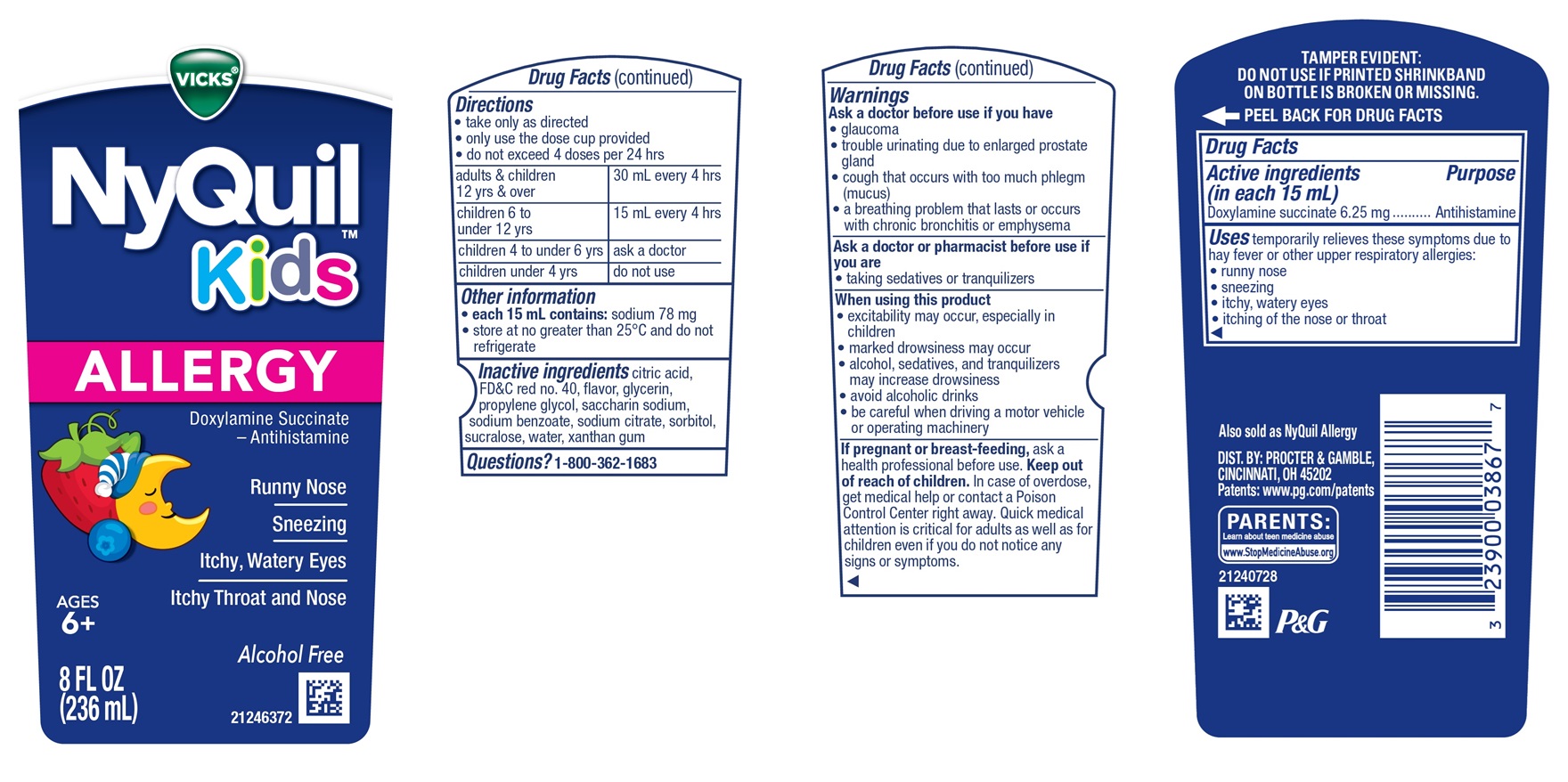 DRUG LABEL: Vicks NyQuil Kids ALLERGY
NDC: 84126-345 | Form: LIQUID
Manufacturer: The Procter & Gamble Manufacturing Company
Category: otc | Type: HUMAN OTC DRUG LABEL
Date: 20250307

ACTIVE INGREDIENTS: DOXYLAMINE SUCCINATE 6.25 mg/15 mL
INACTIVE INGREDIENTS: ANHYDROUS CITRIC ACID; FD&C RED NO. 40; PROPYLENE GLYCOL; WATER; SUCRALOSE; SACCHARIN SODIUM; SODIUM BENZOATE; GLYCERIN; SORBITOL; XANTHAN GUM; TRISODIUM CITRATE DIHYDRATE

VICKS® NyQuil™ Kids Allergy

Drug Facts

Active ingredients (in each 15 mL)

Doxylamine succinate 6.25 mg

Purpose

Antihistamine

Uses

temporarily relieves these symptoms due to hay fever or other upper respiratory allergies:

- runny nose
- sneezing
- itchy, watery eyes
- itching of the nose or throat

Ask a doctor before use if you have

- glaucoma
- trouble urinating due to enlarged prostate gland
- cough that occurs with too much phlegm (mucus)
- a breathing problem that lasts or occurs with chronic bronchitis or emphysema

Ask a doctor or pharmacist before use if you are

- taking sedatives or tranquilizers.

When using this product

- excitability may occur, especially in children
- marked drowsiness may occur
- alcohol, sedatives, and tranquilizers may increase drowsiness
- avoid alcoholic drinks
- be careful when driving a motor vehicle or operating machinery

If pregnant or breast-feeding,

ask a health professional before use.

OVERDOSAGE

In case of overdose, get medical help or contact a Poison Control Center right away. Quick medical attention is critical for adults as well as for children even if you do not notice any signs or symptoms.

Directions

- take only as directed
- only use the dose cup provided
- do not exceed 4 doses per 24 hrs

adults & children 12 yrs & over | 30 mL every 4 hrs
children 6 to under 12 yrs | 15 mL every 4 hrs
children 4 to under 6 yrs | ask a doctor
children under 4 yrs | do not use

Other information

- each 15 mL contains: sodium 15 mg
- Store at no greater than 25°C (77ºF)

Inactive ingredients

citric acid, FD&C red no. 40, flavor, glycerin, propylene glycol, saccharin sodium, sodium benzoate, sodium citrate, sorbitol, sucralose, water, xanthan gum

Questions?

1-800-362-1683

TAMPER EVIDENT: DO NOT USE IF PRINTED SHRINKBAND ON BOTTLE IS BROKEN OR MISSING.

DIST. BY PROCTER & GAMBLE,
CINCINNATI OH 45202

PRINCIPAL DISPLAY PANEL - 236 ml Bottle Label

VICKS®NyQuil™

Kids

ALLERGY

Doxylamine Succinate

- Antihistamine

Runny Nose

Sneezing

Itchy, Watery Eyes

Itchy Throat and Nose

AGES 6+

Alcohol Free

8 FL OZ (236 mL)